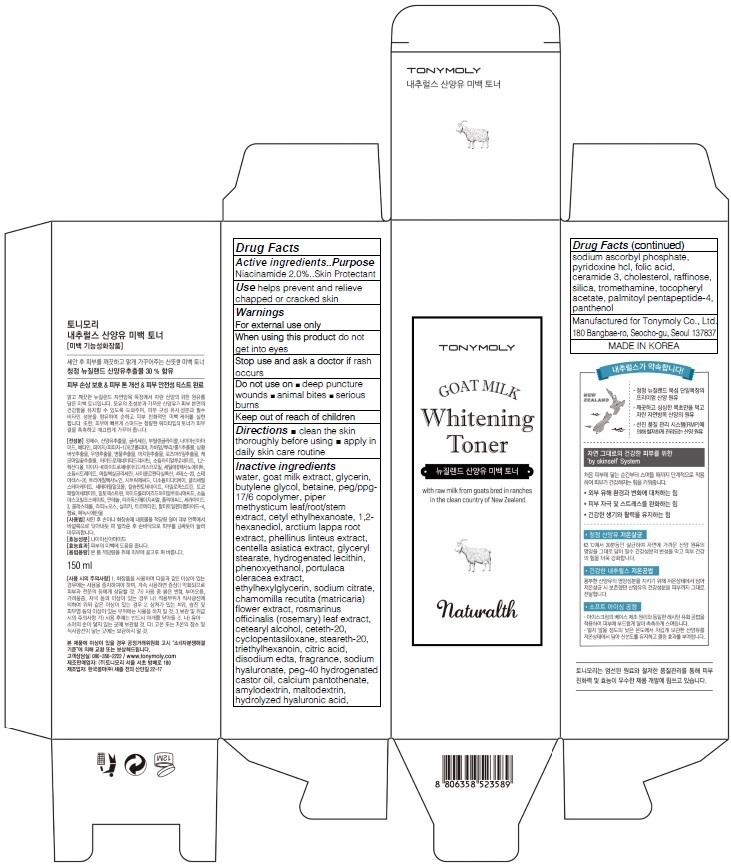 DRUG LABEL: TONYMOLY NATURALTH GOAT MILK WHITENING TONER
NDC: 59078-200 | Form: LIQUID
Manufacturer: TONYMOLY CO.,LTD
Category: otc | Type: HUMAN OTC DRUG LABEL
Date: 20160120

ACTIVE INGREDIENTS: Niacinamide 3.0 g/150 mL
INACTIVE INGREDIENTS: water; goat milk

ACTIVE INGREDIENT

Active ingredients: Niacinamide 2.0%

INACTIVE INGREDIENT

Inactive ingredients: water, goat milk extract, glycerin, butylene glycol, betaine, peg/ppg-17/6 copolymer, piper methysticum leaf/root/stem extract, cetyl ethylhexanoate, 1,2-hexanediol, arctium lappa root extract, phellinus linteus extract, centella asiatica extract, glyceryl stearate, hydrogenated lecithin, phenoxyethanol, portulaca oleracea extract, ethylhexylglycerin, sodium citrate, chamomilla recutita (matricaria) flower extract, rosmarinus officinalis (rosemary) leaf extract, cetearyl alcohol, ceteth-20, cyclopentasiloxane, steareth-20, triethylhexanoin, citric acid, disodium edta, fragrance, sodium hyaluronate, peg-40 hydrogenated castor oil, calcium pantothenate, amylodextrin, maltodextrin, hydrolyzed hyaluronic acid, sodium ascorbyl phosphate, pyridoxine hcl, folic acid, ceramide 3, cholesterol, raffinose, silica, tromethamine, tocopheryl acetate, palmitoyl pentapeptide-4, panthenol

PURPOSE

Purpose: Skin Protectant

WARNINGS

Warnings: For external use only

When using this product do not get into eyes

Stop use and ask a doctor if rash occurs

Do not use on - deep puncture wounds - animal bites - serious burns

Keep out of reach of children

KEEP OUT OF REACH OF CHILDREN

Use

Use: helps prevent and relieve chapped or cracked skin

Directions

Directions: - clean the skin thoroughly before using - apply in daily skin care routine